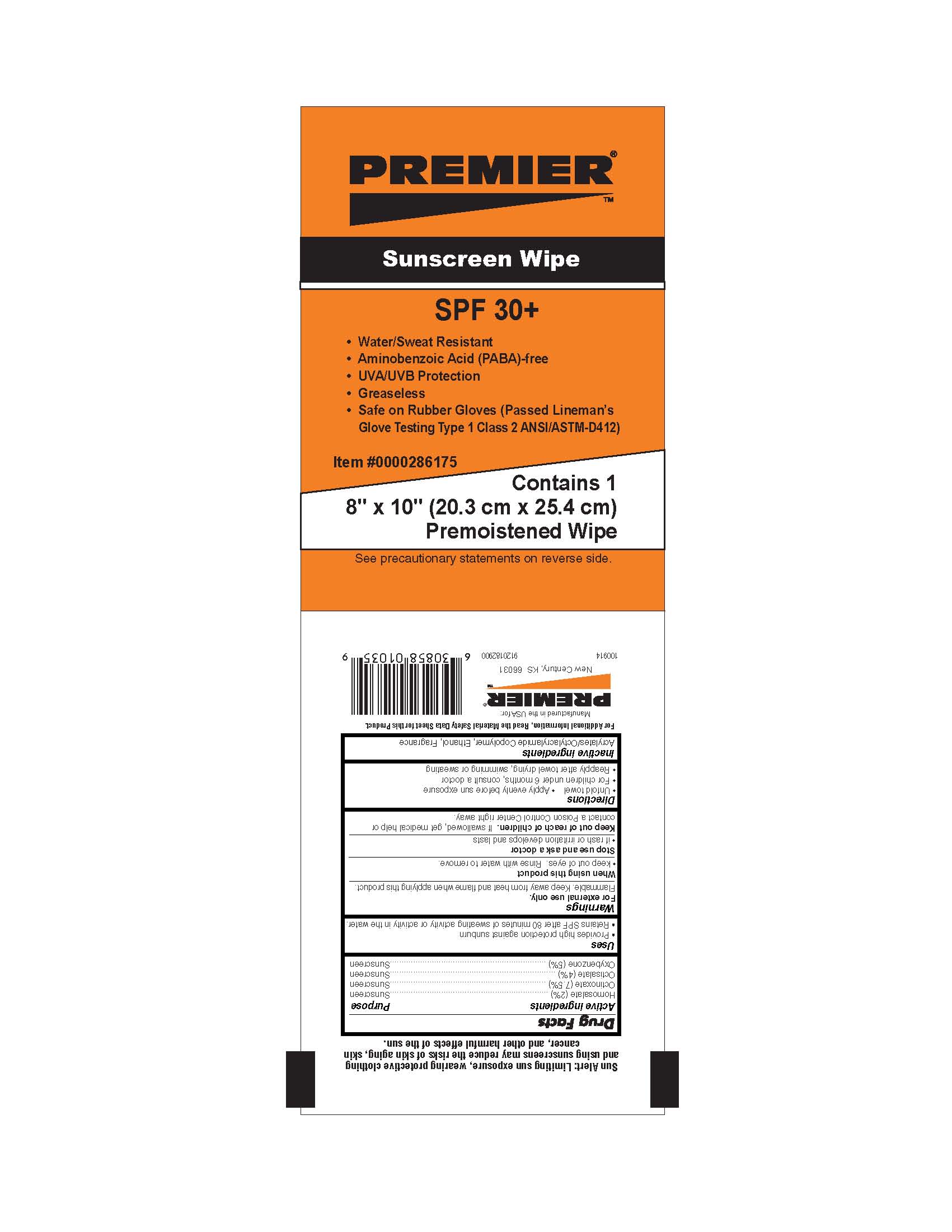 DRUG LABEL: Sunscreen Wipe
NDC: 52648-6175 | Form: CLOTH
Manufacturer: KGP Products, Inc. (dba PREMIER)
Category: otc | Type: HUMAN OTC DRUG LABEL
Date: 20100930

ACTIVE INGREDIENTS: HOMOSALATE 20 g/856 mL; OCTINOXATE 75 g/856 mL; OCTISALATE 40 g/856 mL; OXYBENZONE 50 g/856 mL
INACTIVE INGREDIENTS: ALCOHOL 80.1 g/856 mL

Active Ingredient Purpose

Homosalate (2%)..........................................................................................................Sunscreen

Octinoxate (7.5%).........................................................................................................Sunscreen

Octisalate (4%).............................................................................................................Sunscreen

Oxybenzone (5%)........................................................................................................Sunscreen

Uses

- Provides high protection against sunburn.
- Retains SPF after 80 minutes of sweating or activity in the water.

Warnings

For external use only.

Flammable. Keep away from heat and flame when applying this product.

When using this product

- Keep out of eyes. Rinse with water to remove.

Stop use and ask a doctor

- If rash or irritation develops and lasts.

Keep out of reach of children. If swallowed, get medical help or contact a Poison Control Center right away.

Directions

- Unfold towel.
- Apply evenly before sun exposure.
- For children under 6 months, consult a doctor.
- Reapply after towel drying, swimming or sweating.

QUESTIONS

Inactive Ingredients

Acrylates/Octylacrylamide Copolymer, Ethanol, Fragrance